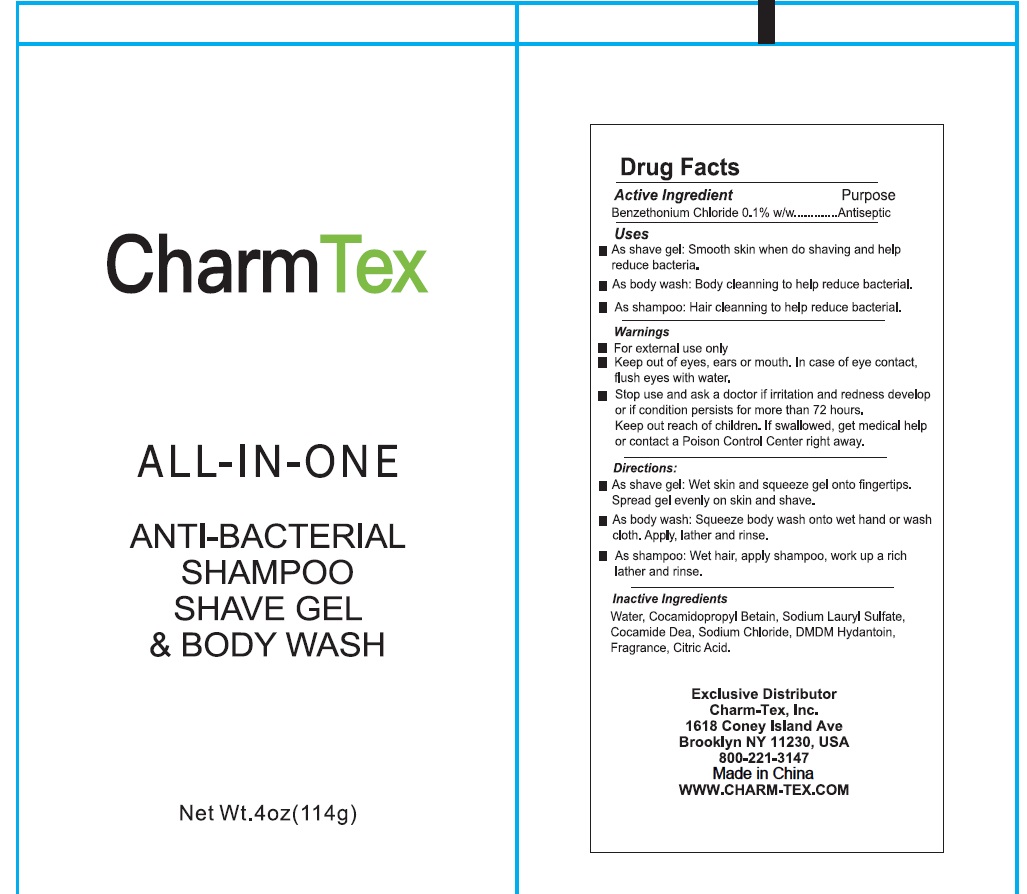 DRUG LABEL: CharmTex All in One Antibacterial Shave Gel Body Wash
NDC: 85420-003 | Form: SHAMPOO
Manufacturer: Liufangjing Biotechnology (Yangzhou) Co., Ltd
Category: otc | Type: HUMAN OTC DRUG LABEL
Date: 20251116

ACTIVE INGREDIENTS: BENZETHONIUM CHLORIDE 0.1 g/100 g
INACTIVE INGREDIENTS: COCAMIDOPROPYL BETAINE; WATER; SODIUM LAURYL SULFATE; COCAMIDE DEA; SODIUM CHLORIDE; DMDM HYDANTOIN; CITRIC ACID

85420-003 All in One antibacterial shave body wash, shampoo

Active Ingredient

Benzethonium Chloride 0.1%

Purpose

Antiseptic

Use

- As shave gel: Smooth skin when do shaving and help reduce bacteria
- As body wash: Body cleaning to help reduce bateria
- As shampoo: Hair cleaning to help redice baterial

Warnings

For external use only

Keep out of eyes, ears, or mouth. In case of contect flush eyes with water

Stop use and ask a doctor if irritation and redness develop, or if condition persists for more than 72 hours

Keep out of reach of children. If swallowed, get medical help or contact a Poison Control Center right away.

Directions

- As shave gel: Wet skin and squeeze gel onto finger tips. Spread gel evenly on skin and shave
- As body wash: Squeeze body wash onto hands or wash cloth. Apply, lather, and rinse
- As shampoo: Wet hair, apply shampoo, work up a rich lather and rinse.

Inactive ingredients

Water, Cocamidepropyl Betain, Sodium Lauyl Sufate, Cocamide Dea, Sodium Chloride, DMDM Hydantoin, Frgrance, Citric Acid